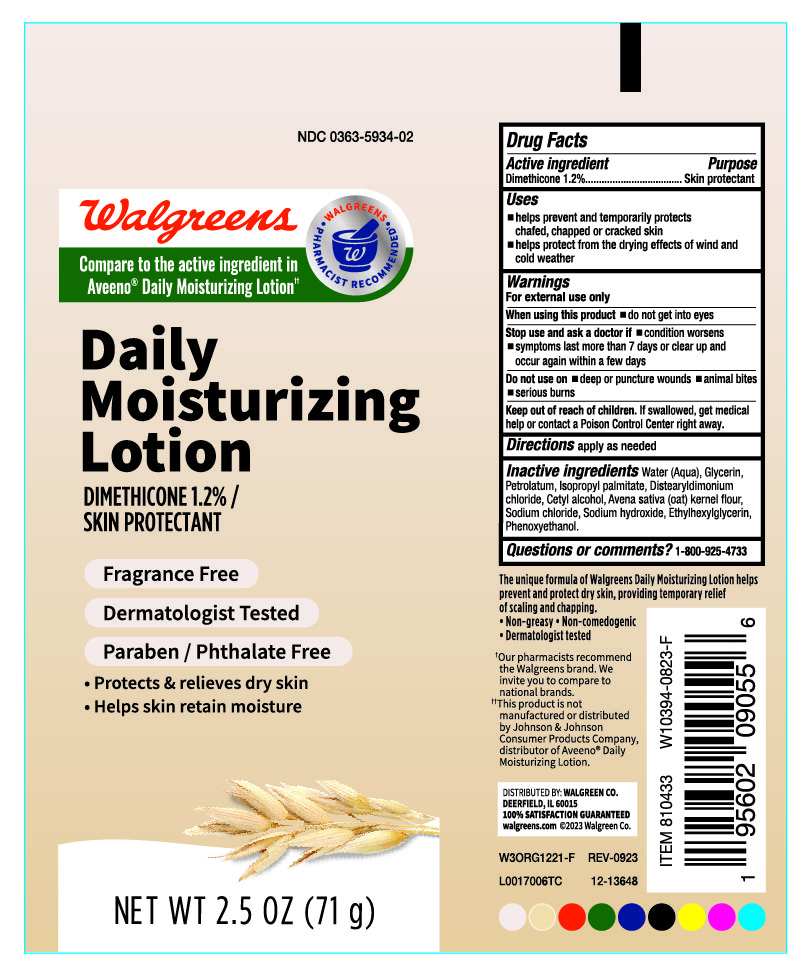 DRUG LABEL: Daily Moisturizer
NDC: 0363-5934 | Form: LOTION
Manufacturer: Walgreens
Category: otc | Type: HUMAN OTC DRUG LABEL
Date: 20240224

ACTIVE INGREDIENTS: DIMETHICONE 1.2 g/100 g
INACTIVE INGREDIENTS: CETYL ALCOHOL; SODIUM CHLORIDE; SODIUM HYDROXIDE; ETHYLHEXYLGLYCERIN; PETROLATUM; ISOPROPYL PALMITATE; WATER; GLYCERIN; PHENOXYETHANOL; DISTEARYLDIMONIUM CHLORIDE; OATMEAL

Walgreens Daily Moisurizing Lotion, NDC 0363-5934-02

Active Ingredient

Dimethicone 1.2%

Purpose

Skin Protectant

Uses

- Helps prevent and temporarily protects chafted, chapped or cracked skin.
- Helps protect from the drying effects of wind and cold weather.

Warnings

For external use only.

When using this product

- do not get into eyes

Stop use and ask a doctor if

- Condition worsens
- Symptoms lasts more than 7 days or clear up and occur again with a few days.

Do not use on

- Deep or puncture wounds
- animal bites
- serious burns

Keep out of reach of children

If swallowed, get medical help or contact Poison Control Center right away.

Directions

Apply as needed.

Inactive Ingredients

Water (Aqua), Glycerin, Petrolatum, Isopropyl Palmatate, Distearyldimonium Chloride, Cetyl Alcohol, Avena Sativa (oat) kernel flour, Sodium Chloride, Sodium Hydroxide, Ethylhexylglycerin, Phenoxyethanol.

Questions or Comments?

1-800-925-4733.